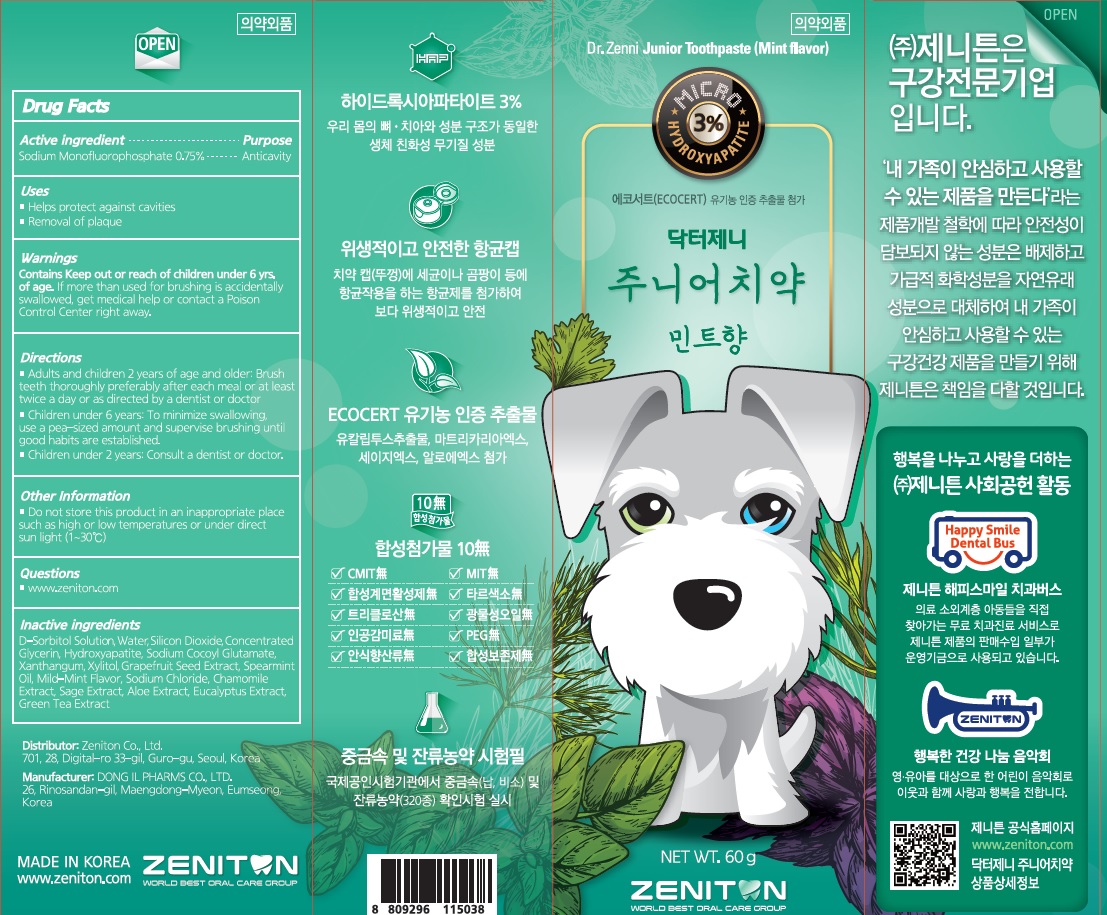 DRUG LABEL: Dr. Zenni Junior Toothpaste(Mint flavor)
NDC: 73029-0003 | Form: PASTE, DENTIFRICE
Manufacturer: Zeniton Co.,Ltd.
Category: otc | Type: HUMAN OTC DRUG LABEL
Date: 20211228

ACTIVE INGREDIENTS: SODIUM MONOFLUOROPHOSPHATE 0.7581 g/100 g
INACTIVE INGREDIENTS: XYLITOL; WATER; SILICON DIOXIDE

ACTIVE INGREDIENT

Sodium Monofluorophosphate 0.75%

PURPOSE

Anticavity

KEEP OUT OF REACH OF CHILDREN

Uses

■ Helps protect against cavities
■ Removal of plaque

WARNINGS

Keep out or reach of children under 6 yrs. of age. If more than used for brushing is accidentally swallowed, get medical help or contact a Poison Control Center right away.

INACTIVE INGREDIENTS

D-Sorbitol Solution, Water, Silicon Dioxide, Concentrated Glycerin, Hydroxyapatite, Sodium Cocoyl Glutamate, Xanthangum, Xylitol, Grapefruit Seed Extract, Spearmint Oil, Mild-Mint Flavor, Sodium Chloride, Chamomile Extract, Sage Extract, Aloe Extract, Eucalyptus Extract, Green Tea Extract

Directions

■ Adults and children 2 years of age and older: Brush teeth thoroughly preferably after each meal or at least twice a day or as directed by a dentist or doctor.
■ Children under 6 years: To minimize swallowing, use a pea-sized amount and supervise brushing until good habits are established.
■ Children under 2 years: Consult a dentist or doctor.

Other Information

■ Do not store this product in an inappropriate place such as high or low temperatures or under direct sun light (1~30℃)

QUESTIONS

■ www.zeniton.com